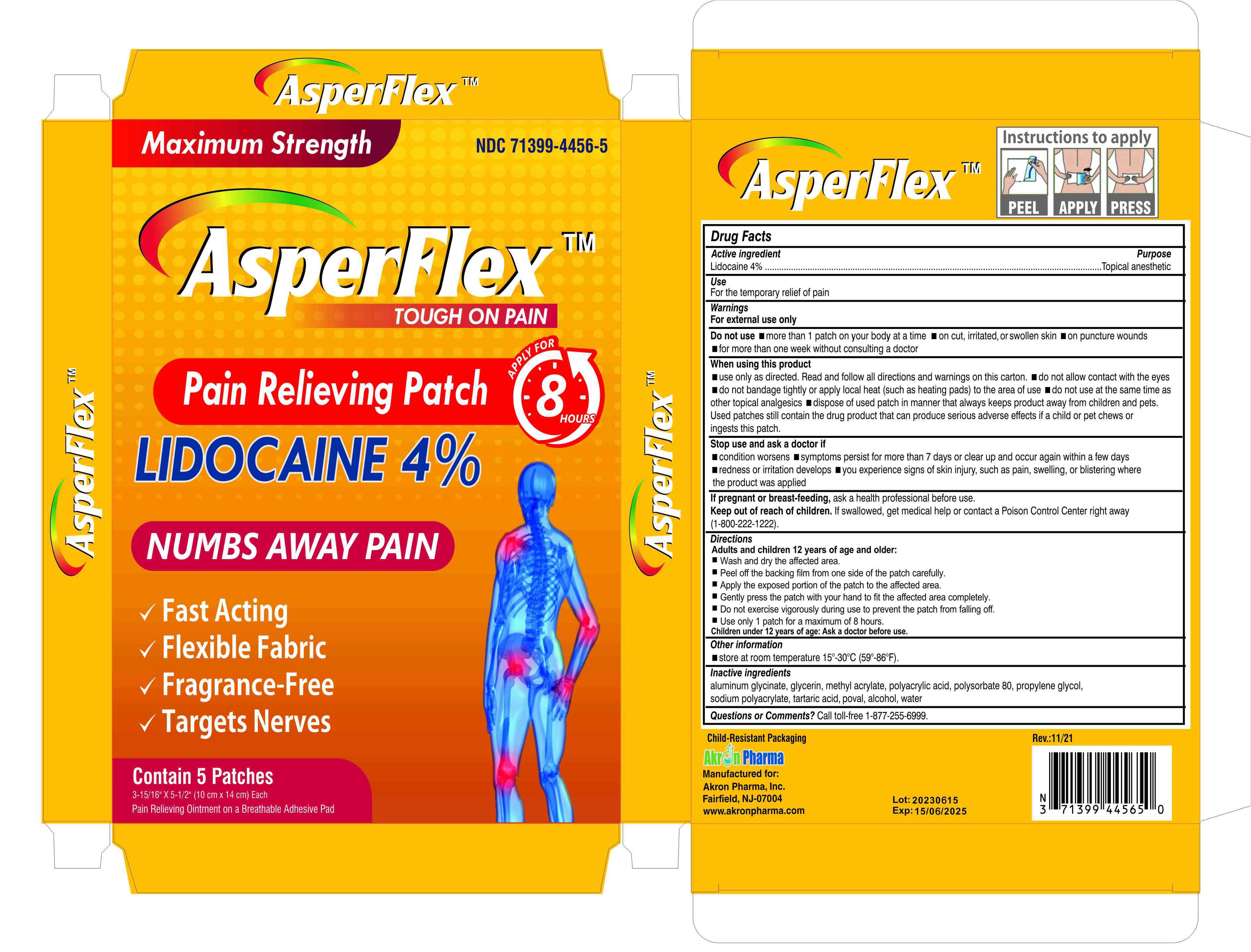 DRUG LABEL: Pain Reliveing Patch
NDC: 81484-601 | Form: PATCH
Manufacturer: Anhui Miao De Tang Pharmaceutical Co., Ltd.
Category: otc | Type: HUMAN OTC DRUG LABEL
Date: 20231018

ACTIVE INGREDIENTS: LIDOCAINE 4 mg/100 1
INACTIVE INGREDIENTS: DIHYDROXYALUMINUM AMINOACETATE ANHYDROUS; PROPYLENE GLYCOL; POLYACRYLIC ACID (250000 MW); TARTARIC ACID; METHYL ACRYLATE; ALCOHOL; WATER; GLYCERIN; POLYSORBATE 80; POLYVINYL ALCOHOL (18000 MW); SODIUM POLYACRYLATE (2500000 MW)

Pain Relieving Patch

LIDOCAINE PATCH 4%

ACTIVE INGREDIENT

Lidocaine 4% Topical anesthetic

PURPOSE

For the temporary relief of pain

INDICATIONS AND USAGE

LIDOCAINE PATCH to help Temporarily relteves minor pain

WARNINGS

For external use only

Do not use more than 1 patch on vour bodv at a time on cut, irritated.or swolen skin on puncture wounds
for more than one week without consulting a doctor

DO NOT USE

use onlv as directed. Read and follow all directions and warnings on this carton. do not allow contact with the eyes
do not bandage tightly or apply local heat (such as heating pads) to the area of use do not use at the same time as other topical analcesics
dispose of used patch in manner that always keeps product away from children and pets. Used patches still contain the drug product that can produce serious adverse effects if a child or pet chews or ingests this patch.

WHEN USING

use onlv as directed. Read and follow all directions and warnings on this carton. do not allow contact with the eyes
do not bandage tightly or apply local heat (such as heating pads) to the area of use do not use at the same time as other topical analcesics
dispose of used patch in manner that always keeps product away from children and pets. Used patches still contain the drug product that can produce serious adverse effects if a child or pet chews or ingests this patch.
lf pregnant or breast-feeding, ask a health professional before use.

STOP USE

condition worsens
symptoms persist for more than 7 days or clear up and occur again within a few days
redness or iritation develops you experience signs of skin injury, such as pain, swelling, or blistering where
the product was applied

Keep out of reach of children. If swallowed, get medical help or contact a Poison Control Center right away(1-800-222-1222).

DOSAGE AND ADMINISTRATION

Adults and children 12 years of age and older:
Wash and dry the affected area.
Peel off the backing film from one side of the patch carefully
Apply the exposed portion of the patch to the affected area.
Gently press the patch with your hand to fit the affected area completely.
Do not exercise vigorously during use to prevent the patch from falling off.
Use only 1 patch for a maximum of 8 hours.
Children under 12 years of age: Ask a doctor before use.

STORAGE AND HANDLING

store at room temperature 15°-30°C (59°-86°F)

INACTIVE INGREDIENT

aluminum glycinate, glycerin, methyl acrylate, polyacrylic acid, polysorbate 80, propylene glycol.
sodium polvacrylate, tartaric acid, poval, alcohol, water